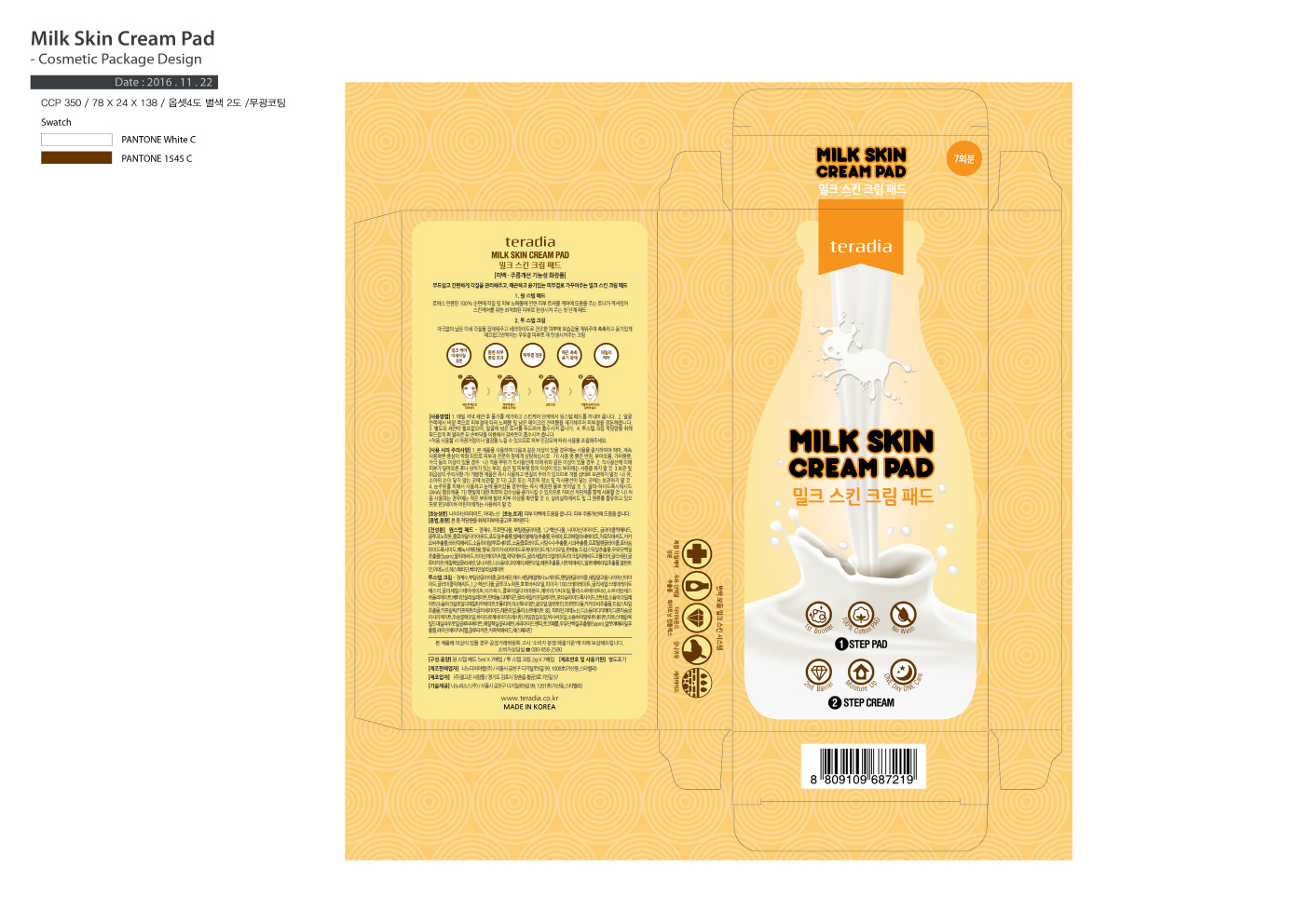 DRUG LABEL: TERADIA MILK SKIN CREAMPAD
NDC: 71483-0004 | Form: CREAM
Manufacturer: NanoDia Lab Co Ltd
Category: otc | Type: HUMAN OTC DRUG LABEL
Date: 20180927

ACTIVE INGREDIENTS: ADENOSINE 0.04 g/100 g; NIACINAMIDE 2 g/100 g
INACTIVE INGREDIENTS: GLYCERIN

Drug Facts

ACTIVE INGREDIENT

Niacinamide, Adenosine

INACTIVE INGREDIENT

Glycerin, etc

PURPOSE

Anti-Wrinkle, Whitening

keep out of reach of the children

INDICATIONS AND USAGE

1. Sweep the face with the one step pad after cleansing.
2. Absorbe the toner of the pad on the skin.
3. Apply the the two step cream on the skin.
4. Absorbe the cream on the skin with palm.

WARNINGS

1. Do not use in the following cases(Eczema and scalp wounds)
2.Side Effects
1)Due to the use of this druf if rash, irritation, itching and symptopms of hypersnesitivity occur dicontinue use and consult your phamacisr or doctor
3.General Precautions
1)If in contact with the eyes, wash out thoroughty with water If the symptoms are servere, seek medical advice immediately
2)This product is for exeternal use only. Do not use for internal use
4.Storage and handling precautions
1)If possible, avoid direct sunlight and store in cool and area of low humidity
2)In order to maintain the quality of the product and avoid misuse
3)Avoid placing the product near fire and store out in reach of children

DOSAGE AND ADMINISTRATION

for external use only